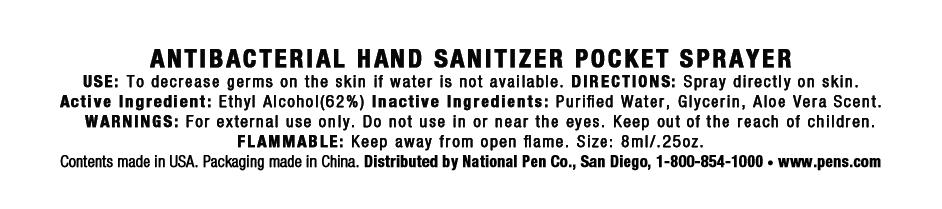 DRUG LABEL: Antibacterial Hand Sanitizer Pocket Sprayer
NDC: 51087-272 | Form: SPRAY
Manufacturer: National Pen Co., LLC
Category: otc | Type: HUMAN OTC DRUG LABEL
Date: 20110203

ACTIVE INGREDIENTS: Alcohol 4.96 mL/8 mL
INACTIVE INGREDIENTS: Glycerin; Water

ANTIBACTERIAL HAND SANITIZER POCKET SPRAYER

Label

ANTIBACTERIAL HAND SANITIZER POCKET SPRAYER

USE: To decrease germs on the skin if water is not available. DIRECTIONS: Spray directly on skin.

Active Ingredient: Ethyl Alcohol (62%) Inactive Ingredients: Purified Water, Glycerin, Aloe Vera Scent.

WARNINGS: For external use only. Do not use in or near the eyes. Keep out of the reach of children.

FLAMMABLE: Keep away from open flame. Size: 8ml/.25oz.

Contents made in USA. Packaging made in China. Distributed by National Pen Co., San Diego, 1-800-854-1000 * www.pens.com

Active Ingredient:

Ethyl Alcohol (62%)

Inactive Ingredients:

Purified Water, Glycerin, Aloe Vera Scent

USE:

To decrease germs on the skin if water is not available.

DIRECTIONS:

Spray directly on skin.

Child Warning:

Keep out of the reach of children.

WARNINGS:

For external use only. Do not use in or near the eyes.

FLAMMABLE: Keep away from open flame.

Size:

8ml/.25oz.